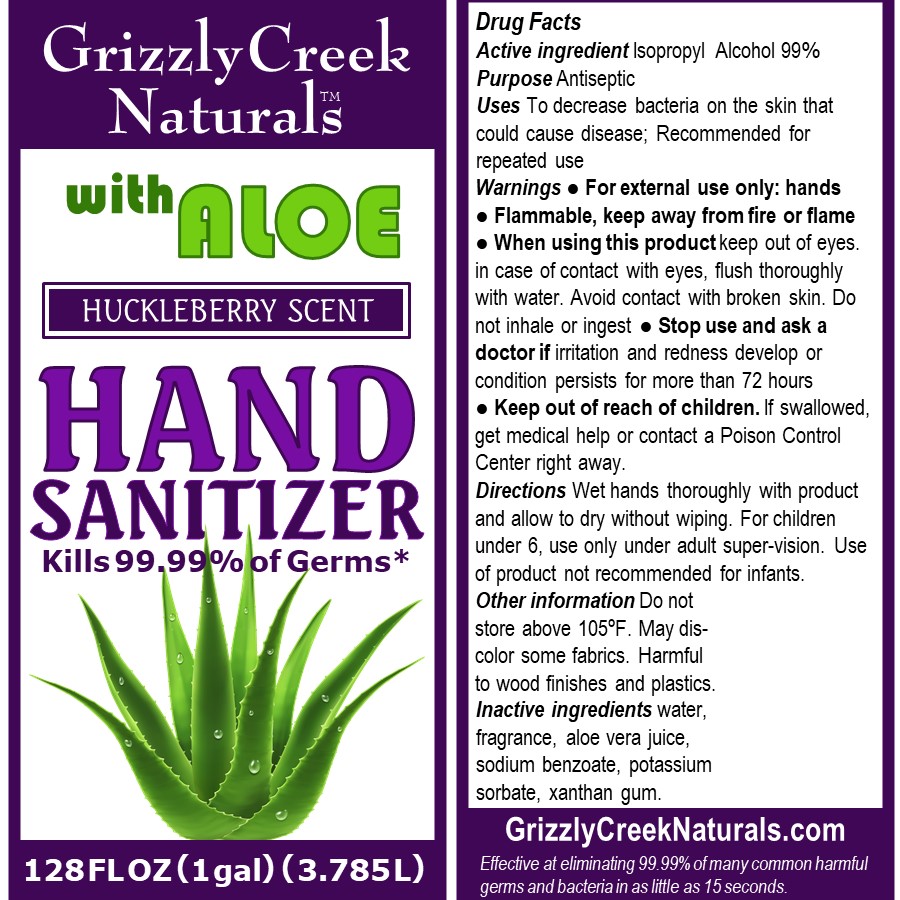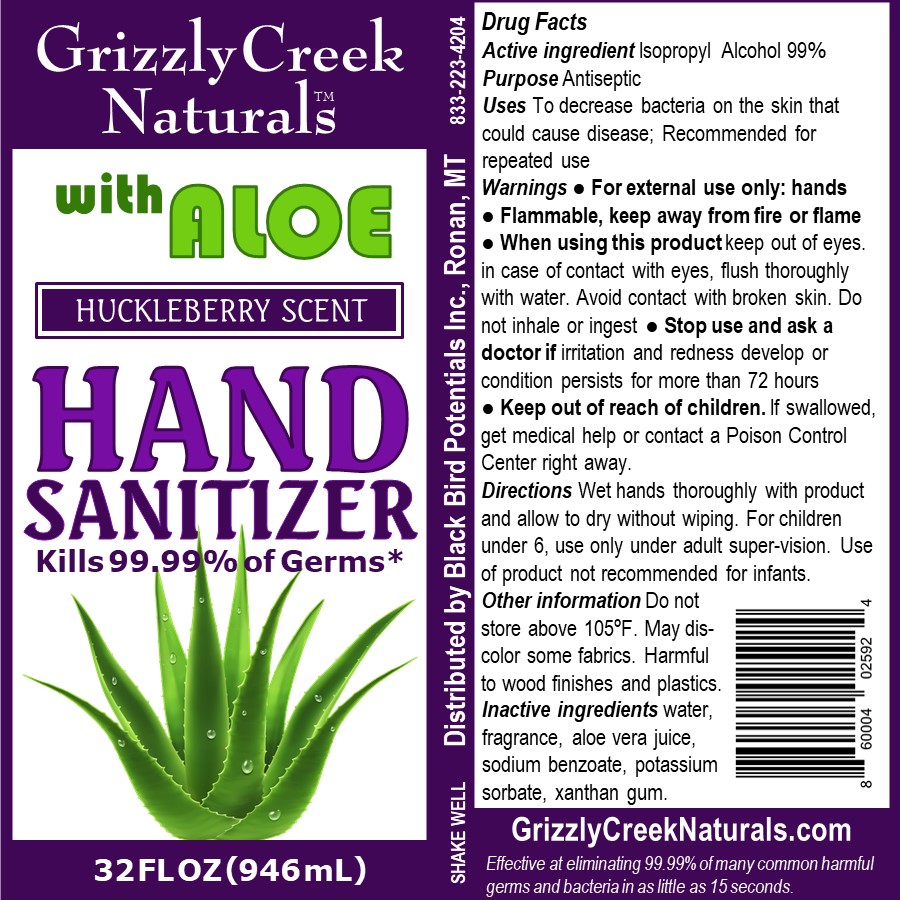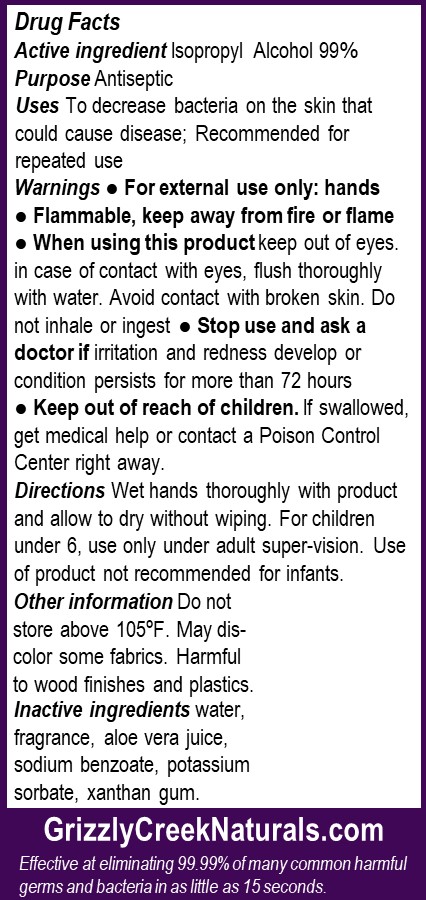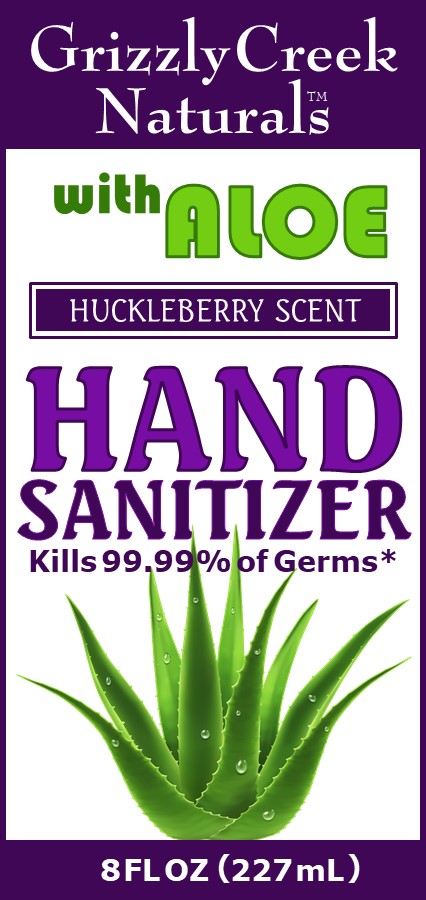 DRUG LABEL: GRIZZLY CREEK NATURALS HAND SANITIZER
NDC: 73816-101 | Form: LIQUID
Manufacturer: BLACK BIRD POTENTIALS INC.
Category: otc | Type: HUMAN OTC DRUG LABEL
Date: 20200527

ACTIVE INGREDIENTS: ISOPROPYL ALCOHOL 0.7 mL/1 mL
INACTIVE INGREDIENTS: SODIUM BENZOATE; POTASSIUM SORBATE; WATER; VACCINIUM MYRTILLUS ANTHOCYANOSIDES; XANTHAN GUM; ALOE ARBORESCENS LEAF

Drug Facts

Active ingredient Isopropyl Alcohol 99%

Purpose Antiseptic

INDICATIONS AND USAGE

Uses To decrease bacteria on the skin that could cause disease; Recommended for repeated use

WARNINGS

Warnings ● For external use only: hands ● Flammable, keep away from fire or flame

● When using this product keep out of eyes. In case of contact with eyes, flush thoroughly with water. Avoid contact with broken skin. Do not inhale or ingest

Stop use and ask a doctor if irritation and redness develop or condition persists for more than 72 hours

Stop use and ask a doctor if irritation and redness develop or condition persists for more than 72 hours

● Keep out of reach of children. If swallowed, get medical help or contact a Poison Control Center right away.

DOSAGE AND ADMINISTRATION

Directions Wet hands thoroughly with product and allow to dry without wiping. For children under 6, use only under adult super-vision. Use of product not recommended for infants.

Other information Do not store above 105ºF. May discolor some fabrics. Harmful to wood finishes and plastics.

INACTIVE INGREDIENT

Inactive ingredients water, fragrance, aloe vera juice, sodium benzoate, potassium sorbate, xanthan gum.

PACKAGE LABEL

227 mL NDC: 73816-101- 02

946 mL NDC: 73816-101-04

227 mL NDC: 73816-101-02

3.875 L NDC: 73816-101-03